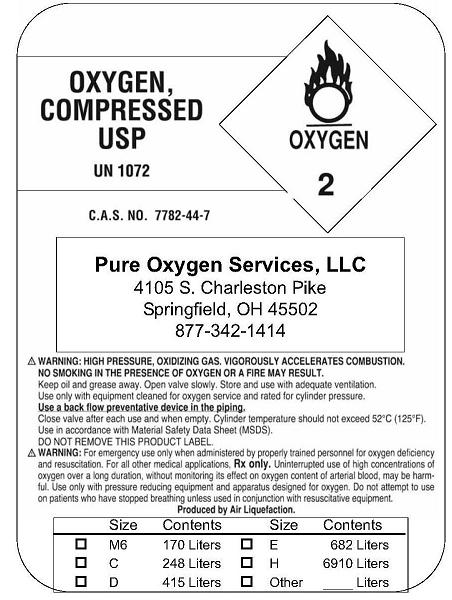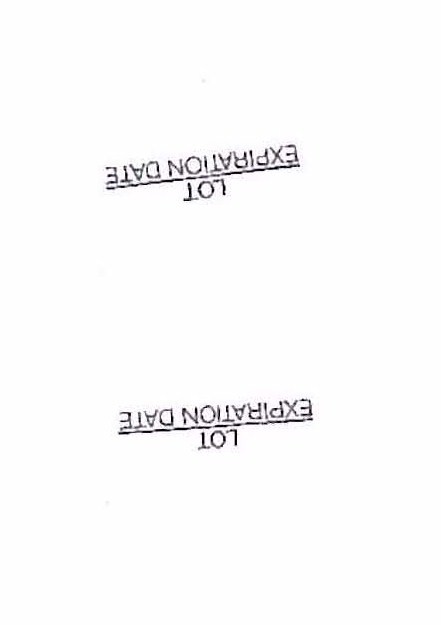 DRUG LABEL: Oxygen
NDC: 50297-0001 | Form: GAS
Manufacturer: Pure Oxygen Services
Category: prescription | Type: HUMAN PRESCRIPTION DRUG LABEL
Date: 20100106

ACTIVE INGREDIENTS: Oxygen 99 L/100 L

Oxygen